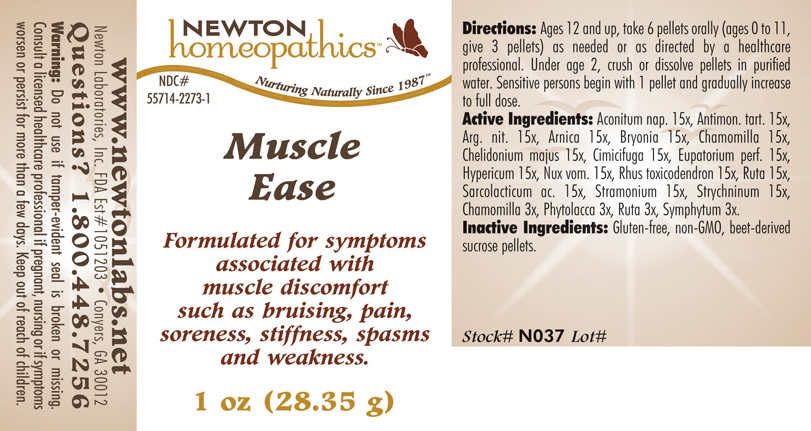 DRUG LABEL: Muscle Ease 
NDC: 55714-2273 | Form: PELLET
Manufacturer: Newton Laboratories, Inc.
Category: homeopathic | Type: HUMAN OTC DRUG LABEL
Date: 20110301

ACTIVE INGREDIENTS: Aconitum Napellus 15 [hp_X]/1 g; Antimony Potassium Tartrate 15 [hp_X]/1 g; Silver Nitrate 15 [hp_X]/1 g; Arnica Montana 15 [hp_X]/1 g; Bryonia Alba Root 15 [hp_X]/1 g; Matricaria Recutita 15 [hp_X]/1 g; Chelidonium Majus 15 [hp_X]/1 g; Black Cohosh 15 [hp_X]/1 g; Eupatorium Perfoliatum Flowering Top 15 [hp_X]/1 g; Hypericum Perforatum 15 [hp_X]/1 g; Strychnos Nux-vomica Seed 15 [hp_X]/1 g; Toxicodendron Pubescens Leaf 15 [hp_X]/1 g; Ruta Graveolens Flowering Top 15 [hp_X]/1 g; Lactic Acid, L- 15 [hp_X]/1 g; Datura Stramonium 15 [hp_X]/1 g; Strychnine 15 [hp_X]/1 g; Phytolacca Americana Root 3 [hp_X]/1 g; Comfrey Root 3 [hp_X]/1 g
INACTIVE INGREDIENTS: Sucrose

Muscle Ease

INDICATIONS & USAGE SECTION

Muscle Ease Formulated for symptoms associated with muscle discomfort such as bruising, pain, soreness, stiffness, spasms and weakness.

DOSAGE & ADMINISTRATION SECTION

Directions: Ages 12 and up, take 6 pellets orally (ages 0 to 11, give 3 pellets) as needed or as directed by a healthcare professional. Under age 2, crush or dissolve pellets in purified water. Sensitive persons begin with 1 pellet and gradually increase to full dose.

OTC - ACTIVE INGREDIENT SECTION

Aconitum nap. 15x, Antimon. tart. 15x, Arg. nit. 15x, Arnica 15x, Bryonia 15x, Chamomilla 15x, Chelidonium majus 15x, Cimicifuga 15x, Eupatorium perf. 15x, Hypericum 15x, Nux vom. 15x, Rhus toxicodendron 15x, Ruta 15x,Sarcolacticum ac. 15x, Stramonium 15x, Strychninum 15x, Chamomilla 3x, Phytolacca 3x, Ruta 3x, Symphytum 3x.

OTC - PURPOSE SECTION

Formulated for symptoms associated with muscle discomfort such as bruising, pain, soreness, stiffness, spasms and weakness.

INACTIVE INGREDIENT SECTION

Inactive Ingredients: Gluten-free, non-GMO, beet-derived sucrose pellets.

QUESTIONS SECTION

www.newtonlabs.net Newton Laboratories, Inc. FDA Est # 1051203 - Conyers, GA 30012
Questions? 1.800.448.7256

WARNINGS SECTION

Warning: Do not use if tamper - evident seal is broken or missing. Consult a licensed healthcare professional if pregnant, nursing or if symptoms worsen or persist for more than a few days. Keep out of reach of children

OTC - PREGNANCY OR BREAST FEEDING SECTION

Consult a licensed healthcare professional if pregnant, nursing or if symptoms worsen or persist for more than a few days.

OTC - KEEP OUT OF REACH OF CHILDREN SECTION

Keep out of reach of children